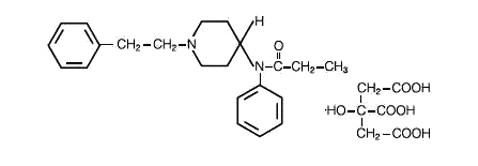 DRUG LABEL: Unknown
Manufacturer: Taylor Pharmaceuticals
Category: prescription | Type: HUMAN PRESCRIPTION DRUG LABELING
Date: 20080421
DEA Schedule: CII

SUBLIMAZE® Injection CII

CII

Rx only

DESCRIPTION

SUBLIMAZE (fentanyl citrate) Injection is a potent narcotic analgesic. Each milliliter of solution contains fentanyl citrate equivalent to 50 mcg of fentanyl base, adjusted to pH 4.0 to 7.5 with sodium hydroxide. SUBLIMAZE is chemically identified as N-(1-phenethyl-4-piperidyl) propionanilide citrate (1:1) with a molecular weight of 528.60. The empirical formula is C22H28N2O • C6H8O7. The structural formula of SUBLIMAZE is:

SUBLIMAZE is a sterile, non-pyrogenic, preservative free aqueous solution for intravenous or intramuscular injection.

CLINICAL PHARMACOLOGY

SUBLIMAZE (fentanyl citrate) is a narcotic analgesic. A dose of 100 mcg (0.1 mg) (2.0 ml) is approximately equivalent in analgesic activity to 10 mg of morphine or 75 mg of meperidine. The principal actions of therapeutic value are analgesia and sedation. Alterations in respiratory rate and alveolar ventilation, associated with narcotic analgesics, may last longer than the analgesic effect. As the dose of narcotic is increased, the decrease in pulmonary exchange becomes greater. Large doses may produce apnea. SUBLIMAZE appears to have less emetic activity than either morphine or meperidine. Histamine assays and skin wheal testing in man indicate that clinically significant histamine release rarely occurs with SUBLIMAZE. Recent assays in man show no clinically significant histamine release in dosages up to 50 mcg/kg (0.05 mg/kg) (1 ml/kg). SUBLIMAZE preserves cardiac stability, and blunts stress-related hormonal changes at higher doses.

The pharmacokinetics of SUBLIMAZE can be described as a three-compartment model, with a distribution time of 1.7 minutes, redistribution of 13 minutes and a terminal elimination half-life of 219 minutes. The volume of distribution for SUBLIMAZE is 4 L/kg.

SUBLIMAZE plasma protein binding capacity decreases with increasing ionization of the drug. Alterations in pH may affect its distribution between plasma and the central nervous system. It accumulates in skeletal muscle and fat, and is released slowly into the blood. SUBLIMAZE, which is primarily transformed in the liver, demonstrates a high first pass clearance and releases approximately 75% of an intravenous dose in urine, mostly as metabolites with less than 10% representing the unchanged drug. Approximately 9% of the dose is recovered in the feces, primarily as metabolites.

The onset of action of SUBLIMAZE is almost immediate when the drug is given intravenously; however, the maximal analgesic and respiratory depressant effect may not be noted for several minutes. The usual duration of action of the analgesic effect is 30 to 60 minutes after a single intravenous dose of up to 100 mcg (0.1 mg) (2.0 ml). Following intramuscular administration, the onset of action is from seven to eight minutes, and the duration of action is one to two hours. As with longer acting narcotic analgesics, the duration of the respiratory depressant effect of SUBLIMAZE may be longer than the analgesic effect. The following observations have been reported concerning altered respiratory response to CO2 stimulation following administration of SUBLIMAZE to man.

1. DIMINISHED SENSITIVITY TO CO2 STIMULATION MAY PERSIST LONGER THAN DEPRESSION OF RESPIRATORY RATE. (Altered sensitivity to CO2 stimulation has been demonstrated for up to four hours following a single dose of 600 mcg (0.6 mg) (12 ml) SUBLIMAZE to healthy volunteers.) SUBLIMAZE frequently slows the respiratory rate, duration and degree of respiratory depression being dose related.
2. The peak respiratory depressant effect of a single intravenous dose of SUBLIMAZE is noted 5 to 15 minutes following injection. See also WARNINGS and PRECAUTIONS concerning respiratory depression.

INDICATIONS AND USAGE

SUBLIMAZE (fentanyl citrate) is indicated:

- for analgesic action of short duration during the anesthetic periods, premedication, induction and maintenance, and in the immediate postoperative period (recovery room) as the need arises.
- for use as a narcotic analgesic supplement in general or regional anesthesia.
- for administration with a neuroleptic as an anesthetic premedication, for the induction of anesthesia and as an adjunct in the maintenance of general and regional anesthesia.
- for use as an anesthetic agent with oxygen in selected high risk patients, such as those undergoing open heart surgery or certain complicated neurological or orthopedic procedures.

CONTRAINDICATIONS

SUBLIMAZE (fentanyl citrate) is contraindicated in patients with known intolerance to the drug or other opioid agonists.

WARNINGS

SUBLIMAZE (fentanyl citrate) SHOULD BE ADMINISTERED ONLY BY PERSONS SPECIFICALLY TRAINED IN THE USE OF INTRAVENOUS ANESTHETICS AND MANAGEMENT OF THE RESPIRATORY EFFECTS OF POTENT OPIOIDS.

AN OPIOID ANTAGONIST, RESUSCITATIVE AND INTUBATION EQUIPMENT AND OXYGEN SHOULD BE READILY AVAILABLE.

See also discussion of narcotic antagonists in PRECAUTIONS and OVERDOSAGE.

If SUBLIMAZE is administered with a tranquilizer, the user should become familiar with the special properties of each drug, particularly the widely differing duration of action. In addition, when such a combination is used, fluids and other countermeasures to manage hypotension should be available.

As with other potent narcotics, the respiratory depressant effect of SUBLIMAZE may persist longer than the measured analgesic effect. The total dose of all narcotic analgesics administered should be considered by the practitioner before ordering narcotic analgesics during recovery from anesthesia. It is recommended that narcotics, when required, should be used in reduced doses initially, as low as ¼ to ⅓ those usually recommended.

SUBLIMAZE may cause muscle rigidity, particularly involving the muscles of respiration. This rigidity has been reported to occur or recur infrequently in the extended postoperative period usually following high dose administration. In addition, skeletal muscle movements of various groups in the extremities, neck and external eye have been reported during induction of anesthesia with fentanyl; these reported movements have, on rare occasions, been strong enough to pose patient management problems. This effect is related to the dose and speed of injection and its incidence can be reduced by: 1) administration of up to ¼ of the full paralyzing dose of a non-depolarizing neuromuscular blocking agent just prior to administration of SUBLIMAZE; 2) administration of a full paralyzing dose of a neuromuscular blocking agent following loss of eyelash reflex when SUBLIMAZE is used in anesthetic doses titrated by slow intravenous infusion; or, 3) simultaneous administration of SUBLIMAZE and a full paralyzing dose of a neuromuscular blocking agent when SUBLIMAZE is used in rapidly administered anesthetic dosages. The neuromuscular blocking agent used should be compatible with the patient's cardiovascular status.

Adequate facilities should be available for postoperative monitoring and ventilation of patients administered anesthetic doses of SUBLIMAZE. Where moderate or high doses are used (above 10 mcg/kg), there must be adequate facilities for postoperative observation, and ventilation if necessary, of patients who have received SUBLIMAZE. It is essential that these facilities be fully equipped to handle all degrees of respiratory depression.

SUBLIMAZE may also produce other signs and symptoms characteristic of narcotic analgesics including euphoria, miosis, bradycardia and bronchoconstriction.

Severe and unpredictable potentiation by MAO inhibitors has been reported for other narcotic analgesics. Although this has not been reported for fentanyl, there are insufficient data to establish that this does not occur with fentanyl. Therefore, when fentanyl is administered to patients who have received MAO inhibitors within 14 days, appropriate monitoring and ready availability of vasodilators and beta-blockers for the treatment of hypertension is indicated.

Head Injuries and Increased Intracranial Pressure

SUBLIMAZE should be used with caution in patients who may be particularly susceptible to respiratory depression, such as comatose patients who may have a head injury or brain tumor. In addition, SUBLIMAZE may obscure the clinical course of patients with head injury.

PRECAUTIONS

General

The initial dose of SUBLIMAZE (fentanyl citrate) should be appropriately reduced in elderly and debilitated patients. The effect of the initial dose should be considered in determining incremental doses.

Nitrous oxide has been reported to produce cardiovascular depression when given with higher doses of SUBLIMAZE.

Certain forms of conduction anesthesia, such as spinal anesthesia and some peridural anesthetics, can alter respiration by blocking intercostal nerves. Through other mechanisms (see CLINICAL PHARMACOLOGY) SUBLIMAZE can also alter respiration. Therefore, when SUBLIMAZE is used to supplement these forms of anesthesia, the anesthetist should be familiar with the physiological alterations involved, and be prepared to manage them in the patients selected for these forms of anesthesia.

When a tranquilizer is used with SUBLIMAZE, pulmonary arterial pressure may be decreased. This fact should be considered by those who conduct diagnostic and surgical procedures where interpretation of pulmonary arterial pressure measurements might determine final management of the patient. When high dose or anesthetic dosages of SUBLIMAZE are employed, even relatively small dosages of diazepam may cause cardiovascular depression.

When SUBLIMAZE is used with a tranquilizer, hypotension can occur. If it occurs, the possibility of hypovolemia should also be considered and managed with appropriate parenteral fluid therapy. Repositioning the patient to improve venous return to the heart should be considered when operative conditions permit. Care should be exercised in moving and repositioning of patients because of the possibility of orthostatic hypotension. If volume expansion with fluids plus other countermeasures do not correct hypotension, the administration of pressor agents other than epinephrine should be considered. Epinephrine may paradoxically decrease blood pressure in patients treated with a neuroleptic that blocks alpha adrenergic activity.

Elevated blood pressure, with and without pre-existing hypertension, has been reported following administration of SUBLIMAZE combined with a neuroleptic. This might be due to unexplained alterations in sympathetic activity following large doses; however, it is also frequently attributed to anesthetic and surgical stimulation during light anesthesia.

When SUBLIMAZE is used with a neuroleptic and the EEG is used for postoperative monitoring, it may be found that the EEG pattern returns to normal slowly.

Many neuroleptic agents have been associated with QT prolongation, torsades de pointes, and cardiac arrest. Neuroleptic agents should be administered with extreme caution in the presence of risk factors for development of prolonged QT syndrome and torsades de pointes, such as: 1) clinically significant bradycardia (less than 50 bpm), 2) any clinically significant cardiac disease, including baseline prolonged QT interval, 3) treatment with Class I and Class III antiarrhythmics, 4) treatment with monoamine oxidase inhibitors (MAOI's), 5) concomitant treatment with other drug products known to prolong the QT interval and 6) electrolyte imbalance, in particular hypokalemia and hypomagnesemia, or concomitant treatment with drugs (e.g. diuretics) that may cause electrolyte imbalance.

ECG monitoring is indicated when a neuroleptic agent is used in conjunction with SUBLIMAZE as an anesthetic premedication, for the induction of anesthesia, or as an adjunct in the maintenance of general or regional anesthesia.

Vital signs should be monitored routinely.

Respiratory depression caused by opioid analgesics can be reversed by opioid antagonists such as naloxone. Because the duration of respiratory depression produced by SUBLIMAZE may last longer than the duration of the opioid antagonist action, appropriate surveillance should be maintained. As with all potent opioids, profound analgesia is accompanied by respiratory depression and diminished sensitivity to CO2 stimulation which may persist into or recur in the postoperative period. Respiratory depression secondary to chest wall rigidity has been reported in the postoperative period. Intraoperative hyperventilation may further alter postoperative response to CO2. Appropriate postoperative monitoring should be employed to ensure that adequate spontaneous breathing is established and maintained in the absence of stimulation prior to discharging the patient from the recovery area.

Impaired Respiration

SUBLIMAZE should be used with caution in patients with chronic obstructive pulmonary disease, patients with decreased respiratory reserve, and others with potentially compromised respiration. In such patients, narcotics may additionally decrease respiratory drive and increase airway resistance. During anesthesia, this can be managed by assisted or controlled respiration.

Impaired Hepatic or Renal Function

SUBLIMAZE should be administered with caution to patients with liver and kidney dysfunction because of the importance of these organs in the metabolism and excretion of drugs.

Cardiovascular Effects

SUBLIMAZE may produce bradycardia, which may be treated with atropine. SUBLIMAZE should be used with caution in patients with cardiac bradyarrhythmias.

Drug Interactions

Other CNS depressant drugs (e.g. barbiturates, tranquilizers, narcotics and general anesthetics) will have additive or potentiating effects with SUBLIMAZE. When patients have received such drugs, the dose of SUBLIMAZE required will be less than usual. Following the administration of SUBLIMAZE, the dose of other CNS depressant drugs should be reduced.

Carcinogenesis, Mutagenesis, Impairment of Fertility

No carcinogenicity or mutagenicity studies have been conducted with SUBLIMAZE. Reproduction studies in rats revealed a significant decrease in the pregnancy rate of all experimental groups. This decrease was most pronounced in the high dosed group (1.25 mg/kg — 12.5X human dose) in which one of twenty animals became pregnant.

Pregnancy

Category C

SUBLIMAZE has been shown to impair fertility and to have an embryocidal effect in rats when given in doses 0.3 times the upper human dose for a period of 12 days. No evidence of teratogenic effects have been observed after administration of SUBLIMAZE to rats. There are no adequate and well-controlled studies in pregnant women. SUBLIMAZE should be used during pregnancy only if the potential benefit justifies the potential risk to the fetus.

Labor and Delivery

There are insufficient data to support the use of SUBLIMAZE in labor and delivery. Therefore, such use is not recommended.

Nursing Mothers

It is not known whether this drug is excreted in human milk. Because many drugs are excreted in human milk, caution should be exercised when SUBLIMAZE is administered to a nursing woman.

Pediatric Use

The safety and efficacy of SUBLIMAZE in children under two years of age have not been established.

Rare cases of unexplained clinically significant methemoglobinemia have been reported in premature neonates undergoing emergency anesthesia and surgery which included the combined use of fentanyl, pancuronium and atropine. A direct cause and effect relationship between the combined use of these drugs and the reported cases of methemoglobinemia has not been established.

ADVERSE REACTIONS

As with other narcotic analgesics, the most common serious adverse reactions reported to occur with SUBLIMAZE (fentanyl citrate) are respiratory depression, apnea, rigidity, and bradycardia; if these remain untreated, respiratory arrest, circulatory depression or cardiac arrest could occur. Other adverse reactions that have been reported are hypertension, hypotension, dizziness, blurred vision, nausea, emesis, diaphoresis, pruritus, urticaria, laryngospasm and anaphylaxis.

It has been reported that secondary rebound respiratory depression may occasionally occur postoperatively. Patients should be monitored for this possibility and appropriate countermeasures taken as necessary.

When a tranquilizer is used with SUBLIMAZE, the following adverse reactions can occur: chills and/or shivering, restlessness, and postoperative hallucinatory episodes (sometimes associated with transient periods of mental depression); extrapyramidal symptoms (dystonia, akathisia, and oculogyric crisis) have been observed up to 24 hours postoperatively. When they occur, extrapyramidal symptoms can usually be controlled with anti-parkinson agents. Postoperative drowsiness is also frequently reported following the use of neuroleptics with SUBLIMAZE.

Cases of cardiac dysrhythmias, cardiac arrest, and death have been reported following the use of SUBLIMAZE with a neuroleptic agent.

DRUG ABUSE AND DEPENDENCE

SUBLIMAZE (fentanyl citrate) is a Schedule II controlled drug substance that can produce drug dependence of the morphine type and therefore has the potential for being abused.

OVERDOSAGE

Manifestations

The manifestations of SUBLIMAZE (fentanyl citrate) overdosage are an extension of its pharmacologic actions (see CLINICAL PHARMACOLOGY) as with other opioid analgesics. The intravenous LD50 of SUBLIMAZE is 3 mg/kg in rats, 1 mg/kg in cats, 14 mg/kg in dogs and 0.03 mg/kg in monkeys.

Treatment

In the presence of hypoventilation or apnea, oxygen should be administered and respiration should be assisted or controlled as indicated. A patent airway must be maintained; an oropharyngeal airway or endotracheal tube might be indicated. If depressed respiration is associated with muscular rigidity, an intravenous neuromuscular blocking agent might be required to facilitate assisted or controlled respiration. The patient should be carefully observed for 24 hours; body warmth and adequate fluid intake should be maintained. If hypotension occurs and is severe or persists, the possibility of hypovolemia should be considered and managed with appropriate parenteral fluid therapy. A specific narcotic antagonist such as nalorphine, levallorphan or naloxone should be available for use as indicated to manage respiratory depression. This does not preclude the use of more immediate countermeasures. The duration of respiratory depression following overdosage of SUBLIMAZE may be longer than the duration of narcotic antagonist action. Consult the package insert of the individual narcotic antagonists for details about use.

DOSAGE AND ADMINISTRATION

50 mcg = 0.05 mg = 1 ml

Dosage should be individualized. Some of the factors to be considered in determining the dose are age, body weight, physical status, underlying pathological condition, use of other drugs, type of anesthesia to be used and the surgical procedure involved. Dosage should be reduced in elderly or debilitated patients (see PRECAUTIONS).

Vital signs should be monitored routinely.

I. Premedication — Premedication (to be appropriately modified in the elderly, debilitated and those who have received other depressant drugs) — 50 to 100 mcg (0.05 to 0.1 mg) (1 to 2 ml) may be administered intramuscularly 30 to 60 minutes prior to surgery.
II. Adjunct to General Anesthesia — See Dosage Range Chart
III. Adjunct to Regional Anesthesia - 50 to 100 mcg (0.05 to 0.1 mg) (1 to 2 ml) may be administered intramuscularly or slowly intravenously, over one to two minutes, when additional analgesia is required.
IV. Postoperatively (recovery room) - 50 to 100 mcg (0.05 to 0.1 mg) (1 to 2 ml) may be administered intramuscularly for the control of pain, tachypnea and emergence delirium. The dose may be repeated in one to two hours as needed.

Usage in Children: For induction and maintenance in children 2 to 12 years of age, a reduced dose as low as 2 to 3 mcg/kg is recommended.

DOSAGE RANGE CHART
TOTAL DOSAGE
Low Dose — 2 mcg/kg (0.002 mg/kg) (0.04 ml/kg) SUBLIMAZE. SUBLIMAZE in small doses is most useful for minor, but painful, surgical procedures. In addition to the analgesia during surgery, SUBLIMAZE may also provide some pain relief in the immediate postoperative period. | Moderate Dose — 2 to 20 mcg/kg (0.002 to 0.02 mg/kg) (0.04 to 0.4 ml/kg) SUBLIMAZE. Where surgery becomes more major, a larger dose is required. With this dose, in addition to adequate analgesia, one would expect to see some abolition of the stress response. However, respiratory depression will be such that artificial ventilation during anesthesia is necessary and careful observation of ventilation postoperatively is essential. | High Dose — 20 to 50 mcg/kg (0.02 to 0.05 mg/kg) (0.4 to 1 ml/kg) SUBLIMAZE. During open heart surgery and certain more complicated neurosurgical and orthopedic procedures where surgery is more prolonged, and in the opinion of the anesthesiologist, the stress response to surgery would be detrimental to the well being of the patient, dosages of 20 to 50 mcg/kg (0.02 to 0.05 mg) (0.4 to 1 ml) of SUBLIMAZE with nitrous oxide/oxygen have been shown to attenuate the stress response as defined by increased levels of circulating growth hormone, catecholamine, ADH and prolactin. When dosages in this range have been used during surgery, postoperative ventilation and observation are essential due to extended postoperative respiratory depression. The main objective of this technique would be to produce "stress free" anesthesia.

DOSAGE RANGE CHART
MAINTENANCE DOSAGE
Low Dose — 2 mcg/kg (0.002 mg/kg) (0.04 ml/kg) SUBLIMAZE. Additional dosages of SUBLIMAZE are infrequently needed in these minor procedures. | Moderate Dose — 2 to 20 mcg/kg (0.002 to 0.02 mg/kg) (0.04 to 0.4 ml/kg) SUBLIMAZE. 25 to 100 mcg (0.025 to 0.1 mg) (0.5 to 2.0 ml) may be administered intravenously or intramuscularly when movement and/or changes in vital signs indicate surgical stress or lightening of analgesia. | High Dose — 20 to 50 mcg/kg (0.02 to 0.05 mcg/kg) (0.4 to 1.0 ml/kg) SUBLIMAZE. Maintenance dosage (ranging from 25 mcg (0.025 mg) (0.5 ml) to one half the initial loading dose) will be dictated by the changes in vital signs which indicate stress and lightening of analgesia. However, the additional dosage selected must be individualized especially if the anticipated remaining operative time is short.

As a General Anesthetic

When attenuation of the responses to surgical stress is especially important, doses of 50 to 100 mcg/kg (0.05 to 0.1 mg/kg) (1 to 2 ml/kg) may be administered with oxygen and a muscle relaxant. This technique has been reported to provide anesthesia without the use of additional anesthetic agents. In certain cases, doses up to 150 mcg/kg (0.15 mg/kg) (3 ml/kg) may be necessary to produce this anesthetic effect. It has been used for open heart surgery and certain other major surgical procedures in patients for whom protection of the myocardium from excess oxygen demand is particularly indicated, and for certain complicated neurological and orthopedic procedures.

As noted above, it is essential that qualified personnel and adequate facilities be available for the management of respiratory depression.

See WARNINGS and PRECAUTIONS for use of SUBLIMAZE (fentanyl citrate) with other CNS depressants, and in patients with altered response.

Parenteral drug products should be inspected visually for particulate matter and discoloration prior to administration, whenever solution and container permit.

HOW SUPPLIED

SUBLIMAZE (fentanyl citrate) Injection is available as:

NDC 11098-030-02 | 50 mcg/ml of fentanyl base, | 2 ml ampoules in packages of 10
NDC 11098-030-05 | 50 mcg/ml of fentanyl base, | 5 ml ampoules in packages of 10
NDC 11098-030-10 | 50 mcg/ml of fentanyl base, | 10 ml ampoules in packages of 5
NDC-11098-030-20 | 50 mcg/ml of fentanyl base, | 20 ml ampoules in packages of 5

STORAGE

Store at 20° to 25°C (68° to 77°F). [See USP Controlled Room Temperature]. PROTECT FROM LIGHT.

TAYLOR PHARMACEUTICALS
AN AKORN COMPANY
Decatur, IL 62522

AFCA0N Rev. 08/05